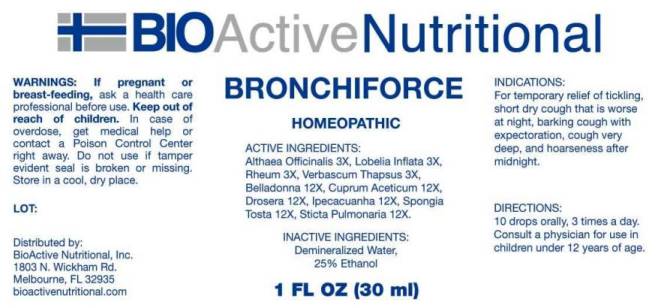 DRUG LABEL: Bronchiforce
NDC: 43857-0544 | Form: LIQUID
Manufacturer: BioActive Nutritional, Inc.
Category: homeopathic | Type: HUMAN OTC DRUG LABEL
Date: 20240802

ACTIVE INGREDIENTS: ALTHAEA OFFICINALIS ROOT 3 [hp_X]/1 mL; LOBELIA INFLATA WHOLE 3 [hp_X]/1 mL; RHEUM PALMATUM ROOT 3 [hp_X]/1 mL; VERBASCUM THAPSUS WHOLE 3 [hp_X]/1 mL; ATROPA BELLADONNA WHOLE 12 [hp_X]/1 mL; CUPRIC ACETATE 12 [hp_X]/1 mL; DROSERA ROTUNDIFOLIA WHOLE 12 [hp_X]/1 mL; IPECAC 12 [hp_X]/1 mL; SPONGIA OFFICINALIS SKELETON, ROASTED 12 [hp_X]/1 mL; LOBARIA PULMONARIA 12 [hp_X]/1 mL
INACTIVE INGREDIENTS: WATER; ALCOHOL

Drug Facts:

ACTIVE INGREDIENTS:

Althaea Officinalis 3X, Lobelia Inflata 3X, Rheum (Palmatum) 3X, Verbascum Thapsus 3X, Belladonna 12X, Cuprum Aceticum 12X, Drosera (Rotundifolia) 12X, Ipecacuanha 12X, Spongia Tosta 12X, Sticta Pulmonaria 12X.

INDICATIONS:

For temporary relief of tickling, short dry cough that is worse at night, barking cough with expectoration, cough very deep, and hoarseness after midnight.

WARNINGS:

If pregnant or breast-feeding, ask a health care professional before use.

Keep out of reach of children. In case of overdose, get medical help or contact a Poison Control Center right away.

Do not use if tamper evident seal is broken or missing.

Store in cool, dry place.

Keep out of reach of children. In case of overdose, get medical help or contact a Poison Control Center right away.

DIRECTIONS:

10 drops orally, 3 times a day. Consult a physician for use in children under 12 years of age.

INDICATIONS:

For temporary relief of tickling, short dry cough that is worse at night, barking cough with expectoration, cough very deep, and hoarseness after midnight.

INACTIVE INGREDIENTS:

Demineralized Water, 25% Ethanol.

QUESTIONS:

Distributed by:
BioActive Nutritional, Inc.
1803 N. Wickham Rd.
Melbourne, FL 32935
bioactivenutritional.com

PACKAGE LABEL DISPLAY:

BIOActive Nutritional

BRONCHIFORCE

HOMEOPATHIC

1 FL OZ (30 ml)